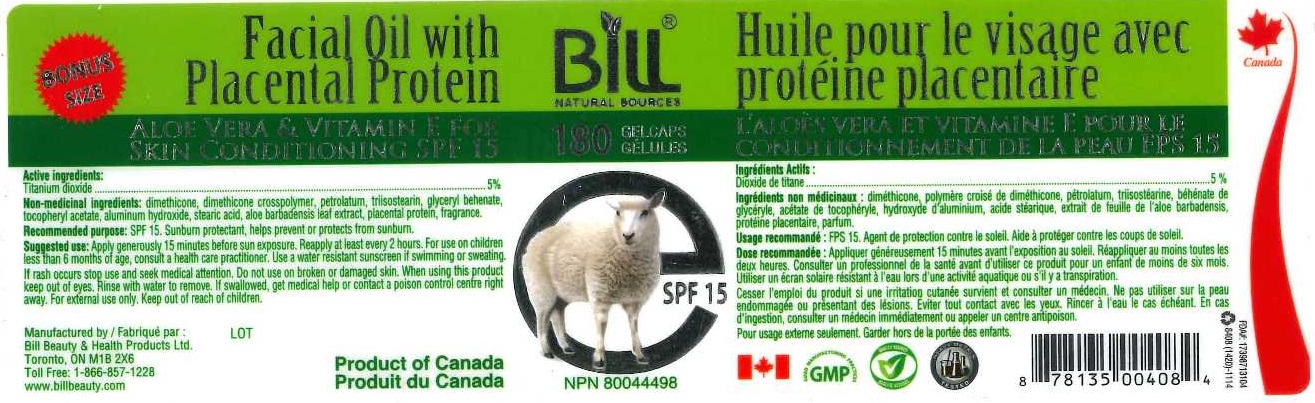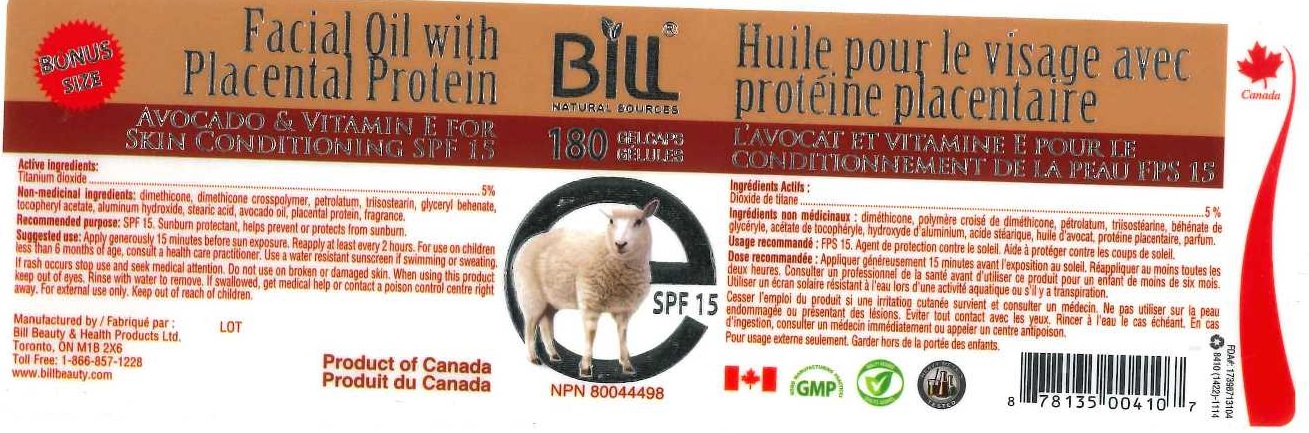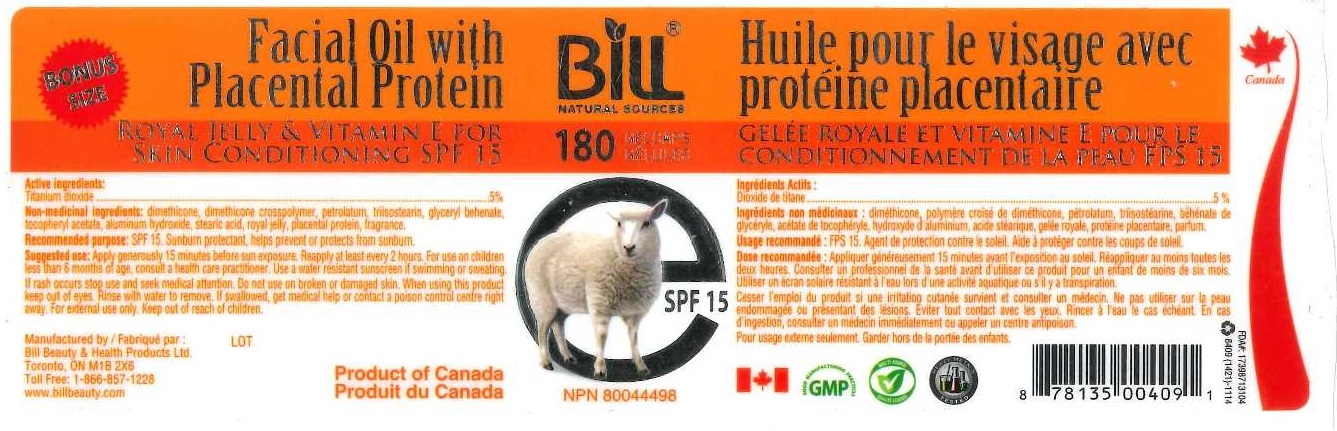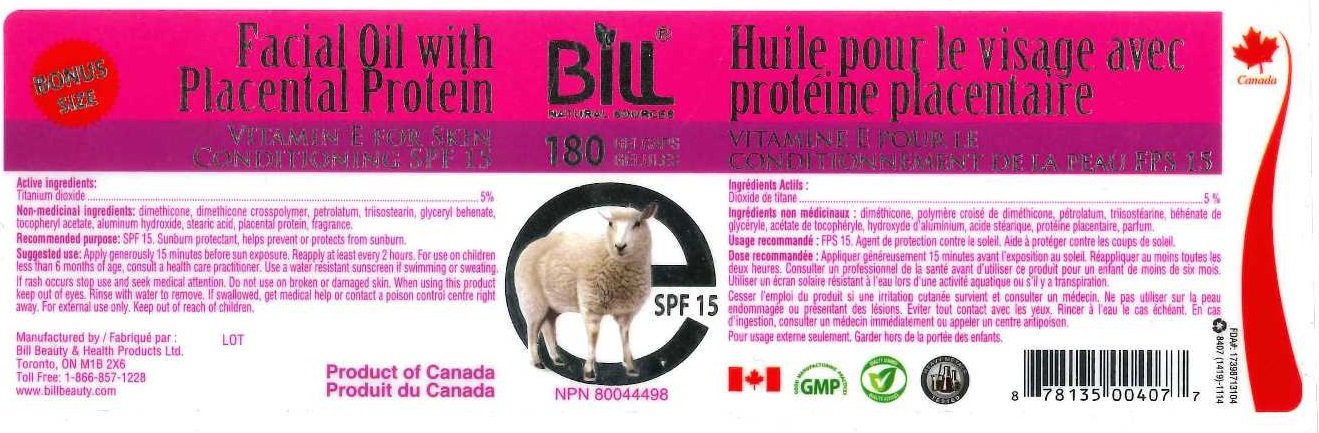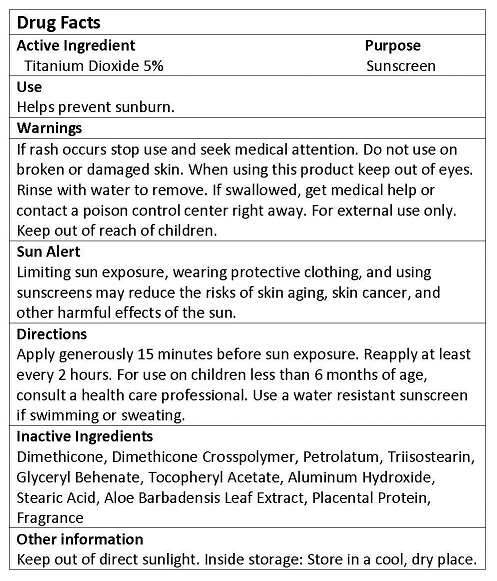 DRUG LABEL: FACIAL WITH PLACENTA PROTEIN
NDC: 70314-201 | Form: OIL
Manufacturer: BILL BEAUTY AND HEALTH PRODUCTS LTD
Category: otc | Type: HUMAN OTC DRUG LABEL
Date: 20160606

ACTIVE INGREDIENTS: TITANIUM DIOXIDE 5 g/100 mL
INACTIVE INGREDIENTS: DIMETHICONE; DIMETHICONE CROSSPOLYMER (450000 MPA.S AT 12% IN CYCLOPENTASILOXANE); TRIISOSTEARIN; PETROLATUM; GLYCERYL MONOBEHENATE; .ALPHA.-TOCOPHEROL ACETATE; ALUMINUM HYDROXIDE; STEARIC ACID; ALOE VERA LEAF; OVIS ARIES PLACENTA

ACTIVE INGREDIENT

Titanium Dioxide 5%

PURPOSE

SUNSCREEN

USES

Helps prevent sunburn.

WARNINGS

If rash occurs stop use and seek medical attention. Do not use on broken or damaged skin. When using this product keep out of eyes. Rinse with water to remove. If swallowed, get medical help or contact a poison control center right away. For external use only. Keep out of reach of children.

Sun Alert
Limiting sun exposure, wearing protective clothing, and using sunscreens may reduce the risks of skin aging, skin cancer, and other harmful effects of the sun.

DIRECTIONS

Apply generously 15 minutes before sun exposure. Reapply at least every 2 hours. For use on children less than 6 months of age, consult a health care professional. Use a water resistant sunscreen if swimming or sweating.

INACTIVE INGREDIENTS

Dimethicone, Dimethicone Crosspolymer, Petrolatum, Triisostearin, Glyceryl Behenate, Tocopheryl Acetate, Aluminum Hydroxide, Stearic Acid, Aloe Barbadensis Leaf Extract, Placental Protein, Fragrance